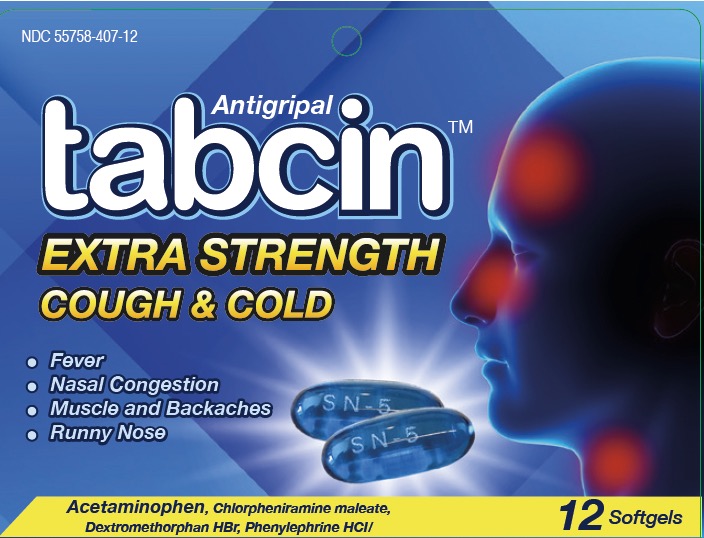 DRUG LABEL: Tabcin
NDC: 55758-407 | Form: CAPSULE, LIQUID FILLED
Manufacturer: Pharmadel LLC
Category: otc | Type: HUMAN OTC DRUG LABEL
Date: 20251205

ACTIVE INGREDIENTS: ACETAMINOPHEN 250 mg/1 1; PHENYLEPHRINE HYDROCHLORIDE 5 mg/1 1; CHLORPHENIRAMINE MALEATE 2 mg/1 1; DEXTROMETHORPHAN HYDROBROMIDE 10 mg/1 1
INACTIVE INGREDIENTS: FD&C BLUE NO. 1; GELATIN; GLYCERIN; POLYETHYLENE GLYCOL 400; POVIDONE K30; PROPYLENE GLYCOL; SORBITOL; WATER; TITANIUM DIOXIDE; METHYLPARABEN; PROPYLPARABEN

Tabcin Antigrip Softgel (HHH)(DA)

Active Ingredients & Purposes

Acetaminophen 250mg

Chlorpheniramine maleate 2 mg

Dextromethorphan hydrobromide 10 mg

Phenylephrine hydrochloride 5 mg

PURPOSE

Active Ingredients | Purposes
Acetaminophen 250mg................................... | Pain reliever/ fever reducer
Chlorpheniramine maleate 2 mg.................... | Antihistamine
Dextromethorphan hydrobromide 10 mg........ | Cough suppressant
Phenylephrine hydrochloride 5 mg.................. | Nasal decongestant

Uses

For the temporary relief of symptoms due to the common cold/ flu:

- runny nose
- sneezing
- cough due to minor bronchial irritation
- nasal congestion
- minor aches and pain
- headache
- sore throat
- and to reduce fever

Warnings

Liver warning

This product contains acetaminophen. Severe liver damage may occur if you take

- more than 10 softgels in 24 hours, which is the maximum daily amount for this product
- with other drugs containing acetaminophen
- 3 or more alcoholic drinks every day while using this product

Allergy alert:

Acetaminophen may cause severe skin reactions. Symptoms may include:

- skin reddening
- blisters
- rash

If a skin reaction occurs, stop use and seek medical help right away.

Sore throat warning:

If sore throat is severe, persists for more than 2 days, and is accompanied or followed by fever, headache, rash, nausea, or vomiting, consult a doctor promptly.

Do not use

- with any other drug containing acetaminophen (prescription or nonprescription). If you are not sure whether a drug contains acetaminophen, ask a doctor or pharmacist.
- if you are now taking a prescription monoamine oxidase inhibitor (MAOI) (certain drugs for depression, psychiatric or emotional conditions, or Parkinson's disease), or for 2 weeks after stopping the MAOI drug. If you do not know if your prescription drug contains an MAOI, ask a doctor or pharmacist before taking this product.

Ask a doctor before use if you have

- liver disease
- heart disease
- high blood pressure
- thyroid disease
- diabetes
- glaucoma
- a breathing problem such as emphysema or chronic bronchitis
- difficulty in urination due to enlargement of the prostate gland
- a persistent or chronic cough such as occurs with smoking, asthma, or emphysema, or if cough is accompanied by excessive phlegm (mucus) unless directed by a doctor

Ask a doctor or pharmacist before use if you are

- taking the blood thinning drug warfarin
- taking sedatives or tranquilizers

When using this product

- do not exceed the recommended dosage
- may cause excitability, especially in children
- may cause drowsiness; alcohol, sedatives, and tranquilizers may increase the drowsiness effect avoid alcoholic beverages while taking this product
- use caution when driving a motor vehicle or operating machinery

Stop use and ask a doctor if

- nervousness, dizziness, or sleeplessness occurs
- the pain or cough gets worse or lasts more than 7 days
- fever gets worse or lasts more than 3 days
- redness or swelling is present
- new symptoms occur
- cough comes back or occurs with a rash or headache that lasts.

These could be signs of a serious condition.

If pregnant or breast-feeding,

ask a health professional before use.

Keep out of reach of children.

In case of overdose, get medical help or contact a Poison Control Center right away. Prompt medical attention is critical for adults as well as for children even if you do not notice any signs or symptoms.

Directions

- adults and children 12 years and over: take 2 softgels with water every 4 hours. Do not exceed 10 softgels in 24 hours or as directed by a doctor.
- children under 12 years: do not use

Other information

- store at room temperature 15°-30°C (59°F-86°F)
- avoid excessive heat

Inactive ingredients

FD&C blue no.1, gelatin, glycerin, polyethylene glycol 400, povidone k30, propylene glycol, propylparaben, methylparaben, sodium hydroxide, sorbitol, titanium dioxide, water

Questions or comments

1-866-359-3478 (M-F) 9 AM to 5 PM EST or www.pharmadel.com